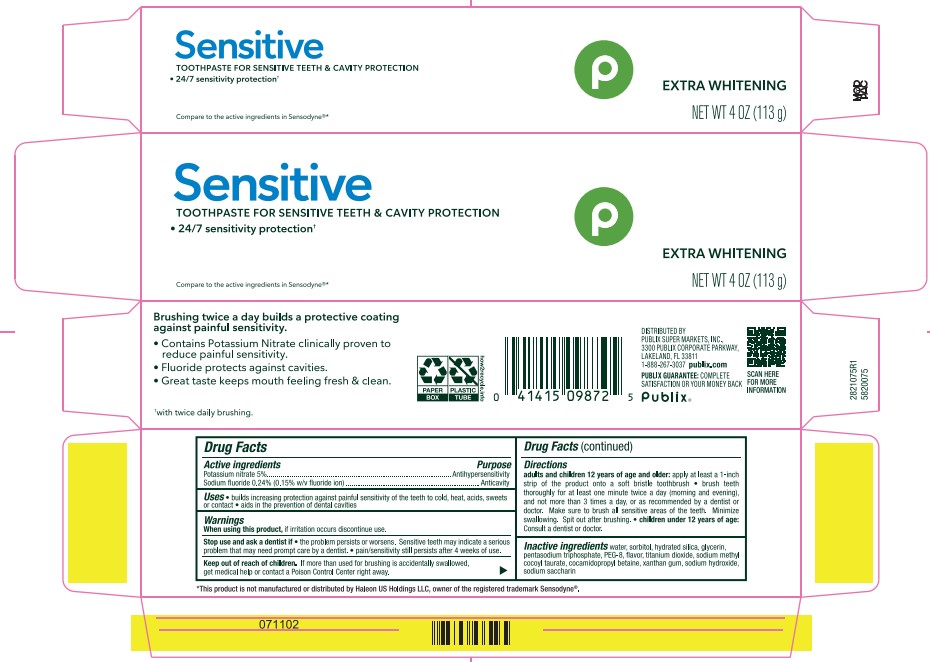 DRUG LABEL: Sensitive Extra Whitening
NDC: 56062-413 | Form: PASTE, DENTIFRICE
Manufacturer: Publix Super Market
Category: otc | Type: HUMAN OTC DRUG LABEL
Date: 20251113

ACTIVE INGREDIENTS: SODIUM FLUORIDE 0.15 g/100 g; POTASSIUM NITRATE 5 g/100 g
INACTIVE INGREDIENTS: SODIUM HYDROXIDE; POLYETHYLENE GLYCOL 400; HYDRATED SILICA; WATER; GLYCERIN; SODIUM METHYL COCOYL TAURATE; COCAMIDOPROPYL BETAINE; TITANIUM DIOXIDE; XANTHAN GUM; SODIUM TRIPOLYPHOSPHATE ANHYDROUS; SORBITOL

5820075 Publix Sensitive Extra Whitening (8015201)

ACTIVE INGREDIENT

Potassium nitrate 5%

Sodium fluoride 0.24% (0.15% w/v fluoride ion)

PURPOSE

Antihypersensitivity

Anticavity

INDICATIONS AND USAGE

builds increasing protection against painful sensitivity of the teeth to cold, heat, acids, sweets or contact * acids in the prevention of dental cavities

When using this product, if irritation occurs discontinue.

Stop use and ask a dentist if * the problem persists or worsen. Sensitive teeth may indicate a serious problem that may need prompt care by a dentist. * pain/sensitivity still persists after 4 weeks of use.

Keep out of reach of children. If more than used for brushing is accidentally swallowed, get medical help or contact a Poison Center right away.

DOSAGE AND ADMINISTRATION

adults and children 12 years pf age and older: apply at least a 1-inch strip of the product onto a soft bristle toothbrush * brush teeth thoroughly for at least one minute twice a day (morning and evening), and not more than 3 times a day, or as recommended by a dentist or doctor. Make sure to brush all sensitive areas of the teeth. Minimize swallowing. Spit out after brushing. * children under 12 years of age: Consult a dentist or doctor.

INACTIVE INGREDIENT

water, sorbitol, hydrated silica, glycerin, pentasodium triphosphate, PEG-8, flavor, titanium dioixde, sodium methyl cocoyl taurate, cocamidopropyl betaine, xanthan gum, sodium hydroxide, sodium saccharin